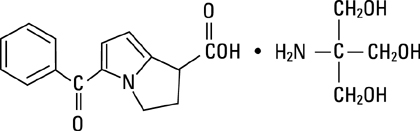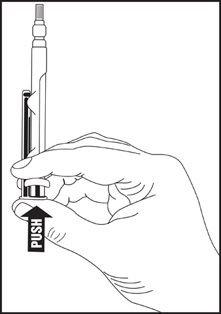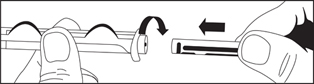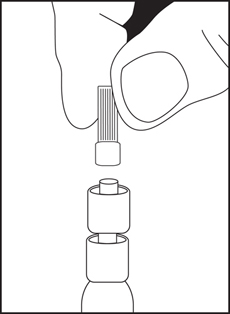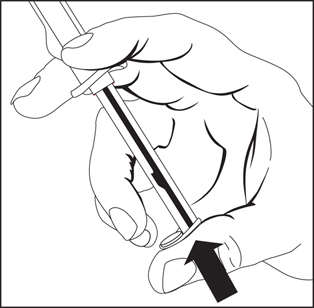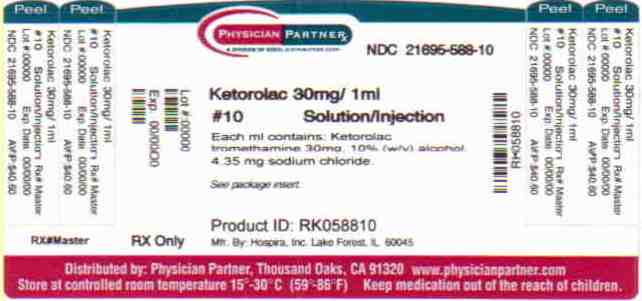 DRUG LABEL: Ketorolac Tromethamine
NDC: 21695-588 | Form: INJECTION, SOLUTION
Manufacturer: Rebel Distributors Corp
Category: prescription | Type: HUMAN PRESCRIPTION DRUG LABEL
Date: 20110117

ACTIVE INGREDIENTS: Ketorolac Tromethamine 30 mg/1 mL
INACTIVE INGREDIENTS: Alcohol; Sodium Chloride 4.35 mg/1 mL; Sodium Hydroxide; Hydrochloric Acid

Ketorolac
Tromethamine
Injection, USP

I.V./I.M.

Rx only

WARNING

Ketorolac tromethamine, a nonsteroidal anti-inflammatory drug (NSAID), is indicated for the short-term (up to 5 days) management of moderately severe acute pain that requires analgesia at the opioid level. It is NOT indicated for minor or chronicpainful conditions. Ketorolac tromethamine is a potent NSAID analgesic, and its administration carries many risks. The resulting NSAID-related adverse events can be serious in certain patients for whom ketorolac tromethamine is indicated, especially when the drug is used inappropriately.Increasing the dose of ketorolac tromethamine beyond the label recommendations will not provide better efficacy but will result in increasing the risk of developing serious adverse events.

Gastrointestinal Effects

Ketorolac tromethamine can cause peptic ulcers, gastrointestinal bleeding, and/or perforation. Therefore, ketorolac tromethamine is CONTRAINDICATED in patients with active peptic ulcer disease, in patients with recent gastrointestinal bleeding or perforation, and in patients with a history of peptic ulcer disease or gastrointestinal bleeding.

Renal Effects

Ketorolac tromethamine is CONTRAINDICATED in patients with advanced renal impairment and in patients at risk for renal failure due to volume depletion (see WARNINGS).

Risk of Bleeding

Ketorolac tromethamine inhibits platelet function and is, therefore, CONTRAINDICATED in patients with suspected or confirmed cerebrovascular bleeding, patients with hemorrhagic diathesis, incomplete hemostasis, and those at high risk of bleeding (see WARNINGS and PRECAUTIONS).

Ketorolac tromethamine is CONTRAINDICATED as prophylactic analgesic before any major surgery, and is CONTRAINDICATED intraoperatively when hemostasis is critical because of the increased risk of bleeding.

Hypersensitivity

Hypersensitivity reactions, ranging from bronchospasm to anaphylactic shock, have occurred and appropriate counteractive measures must be available when administering the first dose of ketorolac tromethamine injection (see CONTRAINDICATIONS and WARNINGS). Ketorolac tromethamine is CONTRAINDICATED in patients with previously demonstrated hypersensitivity to ketorolac tromethamine or allergic manifestations to aspirin or other nonsteroidal anti-inflammatory drugs (NSAIDs).

Intrathecal or Epidural Administration

Ketorolac tromethamine is CONTRAINDICATED for intrathecal or epidural administration due to its alcohol content.

Labor, Delivery and Nursing

The use of ketorolac tromethamine in labor and delivery is CONTRAINDICATED because it may adversely affect fetal circulation and inhibit uterine contractions.

The use of ketorolac tromethamine is CONTRAINDICATED in nursing mothers because of the potential adverse effects of prostaglandin-inhibiting drugs on neonates.

Concomitant Use with NSAIDs

Ketorolac tromethamine is CONTRAINDICATED in patients currently receiving ASA or NSAIDs because of the cumulative risk of inducing serious NSAID-related side effects.

DOSAGE AND ADMINISTRATION

Ketorolac Tromethamine Tablets

Ketorolac tromethamine tablets are indicated only as continuation therapy to ketorolac tromethamineIV/IM, and the combined duration of use of ketorolac tromethamineIV/IM and ketorolac tromethamine tablets is not to exceed 5 (five) days, because of the increased risk of serious adverse events.

The recommended total daily dose of ketorolac tromethamine tablets (maximum 40 mg) is significantly lower than for ketorolac tromethamineIV/IM (maximum 120 mg) (see DOSAGE AND ADMINISTRATION).

Special Populations

Dosage should be adjusted for patients 65 years or older, for patients under 50 kg (110 lbs) of body weight (see DOSAGE AND ADMINISTRATION), and for patients with moderately elevated serum creatinine (see WARNINGS). IV/IM doses of ketorolac tromethamine injection are not to exceed 60 mg (total dose per day) in these patients. Ketorolac tromethamine injection is indicated as a single dose therapy in pediatric patients (see DOSAGE AND ADMINISTRATION); Not to exceed 30 mg for IM administration and 15 mg for IV administration.

DESCRIPTION

Ketorolac tromethamine is a member of the pyrrolo-pyrrole group of nonsteroidal anti-inflammatory drugs (NSAIDs). The chemical name for ketorolac tromethamine is (±)-5-benzoyl-2, 3-dihydro-1H-pyrrolizine-1-carboxylic acid, compound with 2-amino-2-(hydroxymethyl)-1,3-propanediol, and the structural formula is:

Ketorolac tromethamine is a racemic mixture of [-]S and [+]R ketorolac tromethamine. Ketorolac tromethamine may exist in three crystal forms. All forms are equally soluble in water. Ketorolac tromethamine has a pKa of 3.5 and an n-octanol/water partition coefficient of 0.26. The molecular weight of ketorolac tromethamine is 376.41 and the molecular formula is C19H24N2O6.

Ketorolac tromethamine is available for intravenous (IV) or intramuscular (IM) administration as: 15 mg in 1 mL (1.5%), 30 mg in 1 mL (3%) in sterile solutions; 60 mg in 2 mL (3%) of ketorolac tromethamine in sterile solution is available for IM administration only. The solutions contain 10% (w/v) alcohol, and 6.68 mg, 4.35 mg, and 8.70 mg, respectively, of sodium chloride in sterile water. The pH is adjusted with sodium hydroxide and/or hydrochloric acid, and the solutions are packaged with nitrogen. The sterile solutions are clear and slightly yellow in color.

CLINICAL PHARMACOLOGY

PHARMACODYNAMICS

Ketorolac tromethamine is a nonsteroidal anti-inflammatory drug (NSAID) that exhibits analgesic activity in animal models. Ketorolac tromethamine inhibits synthesis of prostaglandins and may be considered a peripherally-acting analgesic. The biological activity of ketorolac tromethamine is associated with the S-form. Ketorolac tromethamine possesses no sedative or anxiolytic properties.

The peak analgesic effect of ketorolac tromethamine occurs within 2 to 3 hours and is not statistically significantly different over the recommended dosage range of ketorolac tromethamine. The greatest difference between large and small doses of ketorolac tromethamine by either route is in the duration of analgesia.

PHARMACOKINETICS

Ketorolac tromethamine is a racemic mixture of [-]S- and [+]R-enantiomeric forms, with the S-form having analgesic activity.

Comparison of IV, IM and Oral Pharmacokinetics

The pharmacokinetics of ketorolac tromethamine, following IV, IM and oral doses of ketorolac tromethamine, are compared in Table 1. In adults, the extent of bioavailability following administration of the oral and IM forms of ketorolac tromethamine was equal to that following an IV bolus.

Linear Kinetics

In adults, following administration of single oral, IM or IV dosesof ketorolac tromethamine, in the recommended dosage ranges, the clearance of the racemate does not change. This implies that the pharmacokinetics of ketorolac tromethamine in adults, following single or multiple IM, IV, or recommended oral doses of ketorolac tromethamine, are linear. At the higher recommended doses, there is a proportional increase in the concentrations of free and bound racemate.

Distribution

The mean apparent volume (Vβ) of ketorolac tromethamine following complete distribution was approximately 13 liters. This parameter was determined from single-dose data.

The ketorolac tromethamine racemate has been shown to be highly protein-bound (99%). Nevertheless, even plasma concentrations as high as 10 mcg/mL will only occupy approximately 5% of the albumin binding sites. Thus, the unbound fraction for each enantiomer will be constant over the therapeutic range. A decrease in serum albumin, however, will result in increased free drug concentrations.

Ketorolac tromethamine is excreted in human milk (see PRECAUTIONS: Lactation and Nursing).

Metabolism

Ketorolac tromethamine is largely metabolized in the liver. The metabolic products are hydroxylated and conjugated forms of the parent drug. The products of metabolism, and some unchanged drug, are excreted in the urine.

Excretion

The principal route of elimination of ketorolac and its metabolites is renal. About 92% of a given dose is found in the urine, approximately 40% as Metabolites and 60% as unchanged ketorolac. Approximately 6% of a dose is excreted in the feces.

A single-dose study with 10 mg ketorolac tromethamine (n=9) demonstrated that the S-enantiomer is cleared approximately two times faster than the R-enantiomer, and that the clearance was independent of the route of administration. This means that the ratio of S/R plasma concentrations decreases with time after each dose. There is little or no inversion of the R- to S- form in humans. The clearance of the racemate in normal subjects, elderly individuals, and in hepatically and renally impaired patients, is outlined in Table 2.

The half-life of the ketorolac tromethamine S-enantiomer was approximately 2.5 hours (SD±0.4) compared with 5 hours (SD±1.7) for the R-enantiomer. In other studies, the half-life for the racemate has been reported to lie within the range of 5 to 6 hours.

Table 1
Table of Approximate Average Pharmacokinetic Parameters (Mean±SD)
Following Oral, Intramuscular and Intravenous Doses of Ketorolac Tromethamine
 | Oral† |  |  |  | Intramuscular* |  |  | Intravenous Bolus‡
Pharmacokinetic; Parameters (units) | 10 mg |  | 15 mg |  | 30 mg |  | 60 mg | 15 mg |  | 30 mg
 | 10 mg |  | 15 mg |  | 30 mg |  | 60 mg | 15 mg |  | 30 mg
Bioavailability (extent) | 100%
Tmax^1 (min) | 44±34 |  | 33±21** |  | 44±29 |  | 33±21** | 1.1±0.7** |  | 2.9±1.8
Cmax^2 (mcg/mL) [Single-dose] | 0.87±0.22 |  | 1.14±0.32** |  | 2.42±0.68 |  | 4.55±1.27** | 2.47±0.51** |  | 4.65±0.96
Cmax (mcg/mL) [steady state qid] | 1.05±0.26** |  | 1.56±0.44** |  | 3.11±0.87** |  | N/A†† | 3.09±1.17** |  | 6.85±2.61
Cmin^3 (mcg/mL) [steady state qid] | 0.29±0.07** |  | 0.47±0.13** |  | 0.93±0.26** |  | N/A | 0.61±0.21** |  | 1.04±0.35
Cavg^4 (mcg/mL) [steady state qid] | 0.59±0.2** |  | 0.94±0.29** |  | 1.88±0.59** |  | N/A | 1.09±0.3** |  | 2.17±0.59
Vβ^5 (L/kg) | —————— 0.175±0.039——————— |  |  |  |  |  |  | 0.210±0.044
% Dose metabolized = <50; % Dose excreted in urine = 91 | % Dose excreted in feces = 6; % Plasma protein binding = 99 |  |  |  |  |  | ^1Time-to-peak plasma concentration; ^2Peak plasma concentration; ^3Trough plasma concentration; ^4Average plasma concentration; ^5Volume of distribution
† Derived from PO pharmacokinetic studies in 77 normal fasted volunteers
*Derived from IM pharmacokinetic studies in 54 normal volunteers
‡ Derived from IV pharmacokinetic studies in 24 normal volunteers
††Not applicable because 60 mg is only recommended as a single dose
**Mean value was simulated from observed plasma concentration data and standard deviation was simulated from percent coefficient of variation for observed Cmax and Tmax data

Table 2
The Influence of Age, Liver and Kidney Function, on the Clearance and
Terminal Half-life of Ketorolac Tromethamine (IM ^1 and ORAL ^2) in Adult Populations
 |  | Total Clearance [in L/h/kg]^3 |  |  |  | Terminal Half-life [in hours]
Type of Subjects |  | IM; Mean (range) |  | ORAL; Mean (range) |  | IM; Mean (range) |  |  | ORAL; Mean (range)
Normal Subjects; IM (n=54); mean age=32, range=18-60; Oral (n=77); mean age=32, range=20-60 |  | 0.023; (0.010-0.046) |  | 0.025; (0.013-0.050) |  | 5.3; (3.5-9.2) |  |  | 5.3; (2.4-9)
Healthy Elderly Subjects; IM (n=13), Oral (n=12); mean age=72, range=65-78 |  | 0.019; (0.013-0.034) |  | 0.024; (0.018-0.034) |  | 7; (4.7-8.6) |  |  | 6.1; (4.3-7.6)
Patients with Hepatic Dysfunction; IM and Oral (n=7); mean age=51, range=43-64 |  | 0.029; (0.013-0.066) |  | 0.033; (0.019-0.051) |  | 5.4; (2.2-6.9) |  |  | 4.5; (1.6-7.6)
Patients with Renal Impairment; IM (n=25), Oral (n=9); serum creatinine=1.9-5.0 mg/dL,; mean age (IM)=54, range=35-71; mean age (Oral)=57, range=39-70 |  | 0.015; (0.005-0.043) |  | 0.016; (0.007-0.052) |  | 10.3; (5.9-19.2) |  |  | 10.8; (3.4-18.9)
Renal Dialysis Patients; IM and Oral (n=9); mean age=40, range=27-63 |  | 0.016; (0.003-0.036) |  | − |  | 13.6; (8-39.1) |  |  | −
^1Estimated from 30 mg single IM doses of ketorolac tromethamine; ^2Estimated from 10 mg single oral doses of ketorolac tromethamine; ^3Liters/hour/kilogram |  |  |  |  |  | IV-Administration: In normal subjects (n=37), the total clearance of 30 mg IV-administered ketorolac tromethamine was 0.030 (0.017-0.051) L/h/kg. The terminal half-life was 5.6 (4-7.9) hours.

Accumulation

Ketorolac tromethamine administered as an IV bolus every 6 hours for 5 days to healthy subjects (n=13), showed no significant difference in Cmax on Day 1 and Day 5. Trough levels averaged 0.29 mcg/mL (SD±0.13) on Day 1 and 0.55 mcg/mL (SD±0.23) on Day 6. Steady state was approached after the fourth dose.

Accumulation of ketorolac tromethamine has not been studied in special populations (geriatric, pediatric, renal failure or hepatic disease patients).

Kinetics in Special Populations

Geriatric Patients

Based on single-dose data only, the half-life of the ketorolac tromethamine racemate increased from 5 to 7 hours in the elderly (65 to 78 years) compared with young healthy volunteers (24 to 35 years) (see Table 2). There was little difference in the Cmax for the two groups (elderly, 2.52 mcg/mL±0.77; young, 2.99 mcg/mL±1.03) (see PRECAUTIONS− Geriatric Use).

Pediatric Patients

Following a single intravenous bolus dose of 0.5 mg/kg in 10 children 4 to 8 years old, the half-life was 6 hours (range: 3.5 to 10 h), the average clearance was 0.042 L/hr/kg and the Vd was 0.26 L/kg (range: 0.19 to 0.44 L/kg). In a second study, following a single intravenous dose of 0.6 mg/kg in 24 children 3 to 18 years old, Cmax was 4.3 ± 1.7 mcg/mL, Tmax was 10.25 ± 1.15 minutes, half-life was 3.8 ± 2.6 hours, Cl was 0.0678 L/hr/kg and Vd was 0.25 L/kg. The volume of distribution and clearance of ketorolac in pediatric patients was twice that observed in adult subjects (see Tables 1 and 2). There are no pharmacokinetic data available for ketorolac tromethamine administration by the IM route in pediatric patients.

Renal Insufficiency

Based on single-dose data only, the mean half-life of ketorolac tromethamine in renally impaired patients is between 6 and 19 hours and is dependent on the extent of the impairment. There is poor correlation between creatinine clearance and total ketorolac tromethamine clearance in the elderly and populations with renal impairment (r=0.5).

In patients with renal disease, the AUC∞ of each enantiomer increased by approximately 100% compared with healthy volunteers. The volume of distribution doubles for the S-enantiomer and increases by 1/5th for the R-enantiomer. The increase in volume of distribution of ketorolac tromethamine implies an increase in unbound fraction.

The AUC∞ ratio of the ketorolac tromethamine enantiomers in healthy subjects and patients remained similar, indicating there was no selective excretion of either enantiomer in patients compared to healthy subjects (see WARNINGS – Renal Effects and Table 2).

Hepatic Insufficiency

There was no significant difference in estimates of half-life, AUC∞ and Cmax in 7 patients with liver disease compared to healthy volunteers (see PRECAUTIONS – Hepatic Effects and Table 2).

Race

Pharmacokinetic differences due to race have not been identified.

CLINICAL STUDIES

Adult Patients

The analgesic efficacy of intramuscularly and intravenously administered ketorolac tromethamine was investigated in two postoperative pain models: general surgery (orthopedic, gynecologic and abdominal) and oral surgery (removal of impacted third molars). The studies were double-blind, single- and multiple-dose, parallel trial designs in patients with moderate to severe pain at baseline. Ketorolac tromethamine injection was compared as follows: IM to meperidine or morphine administered intramuscularly, and IV to morphine administered either directly IV or through a PCA (Patient-Controlled Analgesia) pump.

Short-term Use (up to 5 days) Studies

In adults, the comparisons of intramuscular administration during the first hour, the onset of analgesic action was similar for ketorolac tromethamine and the narcotics, but the duration of analgesia was longer with ketorolac tromethamine than with the opioid comparators meperidine or morphine.

In a multi-dose, postoperative (general surgery) double-blind trial of ketorolac tromethamine 30 mg IM versus morphine 6 and 12 mg IM, each drug given on an “as needed” basis for up to 5 days, the overall analgesic effect of ketorolac tromethamine 30 mg IM was between that of morphine 6 and 12 mg. The majority of patients treated with either ketorolac tromethamine or morphine were dosed for up to 3 days; a small percentage of patients received 5 days of dosing.

In clinical settings where perioperative morphine was allowed, ketorolac tromethamine 30 mg IV, given once or twice as needed, provided analgesia comparable to morphine 4 mg IV once or twice as needed.

There was relatively limited experience with 5 consecutive days of IV-administered ketorolac tromethamine in controlled clinical trials, as most patients were given the drug for 3 days or less. The adverse events seen with IV-administered ketorolac tromethamine were similar to those observed with IM-administered ketorolac tromethamine, as would be expected based on the similar pharmacokinetics and bioequivalence (AUC, clearance, plasma half-life) of IV and IM routes of ketorolac tromethamine administration.

Pediatric Patients

The analgesic efficacy of single doses of ketorolac tromethamine has been demonstrated by showing a decrease in the need for supplemental narcotic in pediatric patients receiving ketorolac as compared to placebo. See discussion of these results under Clinical Studies with Concomitant Use of Opioids below.

Clinical Studies with Concomitant Use of Opioids

Adult Patients

Clinical studies in postoperative pain management have demonstrated that ketorolac tromethamine injection, when used in combination with opioids, significantly reduced opioid consumption. This combination may be useful in the subpopulation of patients especially prone to opioid-related complications. Ketorolac tromethamine and narcotics should not be administered in the same syringe.

In a postoperative study, where all patients received morphine by a PCA device, patients treated with ketorolac tromethamine intravenously as fixed intermittent boluses (e.g., 30 mg initial dose followed by 15 mg q3h), required significantly less morphine (26%) than the placebo group. Analgesia was significantly superior, at various postdosing pain assessment times, in the patients receiving ketorolac tromethamine intravenously plus PCA morphine as compared to patients receiving PCA-administered morphine alone.

Pediatric Patients: Ketorolac tromethamine injection reduced the need for supplemental opioid (fentanyl), when a 1 mg/kg dose was administered immediately following tonsillectomy compared to saline controls (see WARNINGS: Hemorrhage). In another study, when a single bolus dose of 0.9 mg/kg of ketorolac tromethamine injection was given to pediatric patients ages 5 to 12 years, compared to saline, a reduction in supplemental opioid was needed following various surgical procedures. In a third study less supplemental morphine was needed in pediatric patients ages 8 to 16 years, who received a 0.8 mg/kg IV injection of ketorolac tromethamine injection in conjunction with morphine following orthopedic surgical procedures, compared to morphine alone. In a study in pediatric patients ages 3 to 12 years, ketorolac tromethamine injection demonstrated a slower onset of analgesia, but a longer duration of action compared to morphine. There is limited data available to support the use of multiple doses of ketorolac tromethamine injection in pediatric patients. There are also insufficient data available to support the use of ketorolac tromethamine tablets in pediatric patients.

Postmarketing Surveillance Study

A large postmarketing observational, non-randomized study, involving approximately 10,000 patients receiving ketorolac tromethamine, demonstrated that the risk of clinically serious gastrointestinal (G.I.) bleeding was dose-dependent (see Table 3A and 3B.) This was particularly true in elderly patients who received an average dose greater than 60 mg/day of ketorolac tromethamine (Table 3A).

Table 3 Incidence of Clinically Serious G.I. Bleeding as Related to Age, Total Daily Dose, and History of G.I. Perforation, Ulcer, Bleeding (PUB) after up to 5 Days of Treatment with Ketorolac Tromethamine Injection
A. Patients without History of PUB
Age of Patients | Total Daily Dose of Ketorolac Tromethamine Injection
Age of Patients | ≤60 mg | >60 to 90 mg | >90 to 120 mg | >120 mg
<65 years of age | 0.4% | 0.4% | 0.9% | 4.6%
≥65 years of age | 1.2% | 2.8% | 2.2% | 7.7%
B. Patients with History of PUB
Age of Patients | Total Daily Dose of Ketorolac Tromethamine Injection
Age of Patients | ≤60 mg | >60 to 90 mg | >90 to 120 mg | >120 mg
<65 years of age | 2.1% | 4.6% | 7.8% | 15.4%
≥65 years of age | 4.7% | 3.7% | 2.8% | 25%

INDICATIONS AND USAGE

Adult Patients: Ketorolac tromethamine is indicated for the short-term (≤5 days) management of moderately severe, acute pain that requires analgesia at the opioid level, usually in a postoperative setting. Therapy should always be initiated with IV or IM ketorolac tromethamine, and the oral dosage form is to be used only as continuation treatment, if necessary. Combined use of IV/IM and the oral dosage form is not to exceed 5 days of use because of the potential of increasing the frequency and severity of adverse reactions associated with the recommended doses (see WARNINGS, PRECAUTIONS, DOSAGE AND ADMINISTRATION, and ADVERSE REACTIONS). Patients should be switched to alternative analgesics as soon as possible, but ketorolac tromethamine therapy is not to exceed 5 days.

Pediatric Patients: The safety and effectiveness of single doses of ketorolac tromethamine injection have been established in pediatric patients between the ages of 2 and 16 years. Ketorolac tromethamine as a single injectable dose, has been shown to be effective in the management of moderately severe acute pain that requires analgesia at the opioid level, usually in the postoperative setting. There is limited data available to support the use of multiple doses of ketorolac tromethamine injection in pediatric patients. Safety and effectiveness have not been established in pediatric patients below the age of 2 years. Use of ketorolac tromethamine injection in pediatric patients is supported by evidence from adequate and well-controlled studies of ketorolac tromethamine injection in adults with additional pharmacokinetic, efficacy and safety data on its use in pediatric patients available in the published literature (see CLINICAL PHARMACOLOGY: Clinical Studies, WARNINGS, and PRECAUTIONS).

Ketorolac tromethamine injection has been used concomitantly with morphine and meperidine and has shown an opioid-sparing effect. For breakthrough pain, it is recommended to supplement the lower end of the ketorolac tromethamine injection dosage range with low doses of narcotics prn, unless otherwise contraindicated. Ketorolac tromethamine and narcotics should not be administered in the same syringe (see DOSAGE AND ADMINISTRATION −Pharmaceutical Information for Ketorolac Tromethamine Injection).

CONTRAINDICATIONS

(see also Boxed WARNING)

Ketorolac tromethamine is CONTRAINDICATED in patients with active peptic ulcer disease, in patients with recent gastrointestinal bleeding or perforation and in patients with a history of peptic ulcer disease or gastrointestinal bleeding.

Ketorolac tromethamine is CONTRAINDICATED in patients with advanced renal impairment or in patients at risk for renal failure due to volume depletion (see WARNINGS for correction of volume depletion).

Ketorolac tromethamine is CONTRAINDICATED in labor and delivery because, through its prostaglandin synthesis inhibitory effect, it may adversely affect fetal circulation and inhibit uterine contractions, thus increasing the risk of uterine hemorrhage.

The use of ketorolac tromethamine is CONTRAINDICATED in nursing mothers because of the potential adverse effects of prostaglandin-inhibiting drugs on neonates.

Ketorolac tromethamine is CONTRAINDICATED in patients with previously demonstrated hypersensitivity to ketorolac tromethamine, allergic manifestations to aspirin or other nonsteroidal anti-inflammatory drugs (NSAIDs).

Ketorolac tromethamine is CONTRAINDICATED as prophylactic analgesic before any major surgery and is CONTRAINDICATED intraoperatively when hemostasis is critical because of the increased risk of bleeding.

Ketorolac tromethamine inhibits platelet function and is, therefore, CONTRAINDICATED in patients with suspected or confirmed cerebrovascular bleeding, hemorrhagic diathesis, incomplete hemostasis, and those at high risk of bleeding (see WARNINGS and PRECAUTIONS).

Ketorolac tromethamine is CONTRAINDICATED in patients currently receiving ASA or NSAIDs because of the cumulative risks of inducing serious NSAID-related adverse events.

Ketorolac tromethamine injection is CONTRAINDICATED for neuraxial (epidural or intrathecal) administration due to its alcohol content.

The concomitant use of ketorolac tromethamine and probenecid is CONTRAINDICATED.

WARNINGS

(see also Boxed WARNING)

► The combined use of ketorolac tromethamine injection and ketorolac tromethamine tablets is not to exceed 5 days in adults. Only single doses of ketorolac tromethamine injection are recommended for use in pediatric patients.

The most serious risks associated with ketorolac tromethamine are:

- Gastrointestinal (GI) Effects− Risk of GI Ulceration, Bleeding and Perforation: Ketorolac tromethamine is CONTRAINDICATED in patients with previously documented peptic ulcers and/or G.I. bleeding. Serious gastrointestinal toxicity, such as bleeding, ulceration, and perforation, can occur at any time, with or without warning symptoms, in patients treated with ketorolac tromethamine. Studies to date with NSAIDs have not identified any subset of patients not at risk of developing peptic ulceration and bleeding. Elderly or debilitated patients seem to tolerate ulceration or bleeding less well than other individuals, and most spontaneous reports of fatal G.I. events are in this population. Postmarketing experience with parenterally administered ketorolac tromethamine suggests that there may be a greater risk of gastrointestinal ulcerations, bleeding and perforation in the elderly.
- The incidence and severity of gastrointestinal complications increases with increasing dose of, and duration of treatment with ketorolac tromethamine. In a non-randomized, in-hospital postmarketing surveillance study, comparing ketorolac tromethamine injection to parenteral opioids, higher rates of clinically serious G.I. bleeding were seen in patients<65 years of age who received an average total daily dose of more than 90 mg of ketorolac tromethamine injection per day (see CLINICAL PHARMACOLOGY − Postmarketing Surveillance Study).
- The same study showed that elderly (≥65 years of age), and debilitated patients are more susceptible to gastrointestinal complications. A history of peptic ulcer disease was revealed as another risk factor that increases the possibility of developing serious gastrointestinal complications during ketorolac tromethamine therapy (see Tables 3A and 3B).

Hemorrhage: Because prostaglandins play an important role in hemostasis, and NSAIDs affect platelet aggregation as well, use of ketorolac tromethamine in patients who have coagulation disorders should be undertaken very cautiously, and those patients should be carefully monitored. Patients on therapeutic doses of anticoagulants (e.g., heparin or dicumarol derivatives) have an increased risk of bleeding complications if given ketorolac tromethamine concurrently; therefore, physicians should administer such concomitant therapy only extremely cautiously. The concurrent use of ketorolac tromethamine and prophylactic low-dose heparin (2500 to 5000 units q12h), warfarin and dextrans have not been studied extensively, but may also be associated with an increased risk of bleeding. Until data from such studies are available, physicians should carefully weigh the benefits against the risks, and use such concomitant therapy in these patients only extremely cautiously. In patients who receive anticoagulants for any reason, there is an increased risk of intramuscular hematoma formation from IM administered ketorolac tromethamine (see PRECAUTIONS − Drug Interactions). Patients receiving therapy that affects hemostasis should be monitored closely.

In postmarketing experience, postoperative hematomas and other signs of wound bleeding have been reported in associationwith the perioperative use of ketorolac tromethamine injection. Therefore, perioperative use of ketorolac tromethamine should be avoided and postoperative use be undertaken with caution when hemostasis is critical (see WARNINGS and PRECAUTIONS).

Pediatrics and Tonsillectomy: Physicians should consider the increased risk of bleeding before deciding to administer ketorolac tromethamine injection in patients following tonsillectomy. Ketorolac tromethamine injection is not recommended for use in pediatric patients below the age of 2 years. In a retrospective analysis of patients having undergone tonsillectomy with or without adenoidectomy, the risk of bleeding was 10.1% in patients administered ketorolac tromethamine injection compared to 2.2% in those receiving opioids. The postoperative hemorrhage rate in patients 12 years and younger was 6.5% and 3.3% with and without ketorolac tromethamine injection, respectively. In a prospective study of ketorolac tromethamine injection in pediatric patients (ages 3 to 9 years) undergoing tonsillectomy with or without adenoidectomy, the overall incidence of bleeding was similar between the patients receiving ketorolac tromethamine injection and morphine (16.3% versus 17%, respectively). However, during the first 24 hours after surgery, a higher incidence of bleeding was observed in the ketorolac tromethamine injection group (14.3%) versus the morphine group (4.2%).

Anaphylactoid Reactions: Anaphylactoid reactions may occur in patients without a known previous exposure or hypersensitivity to aspirin, ketorolac tromethamine, or other NSAIDs, or in individuals with a history of angioedema, bronchospastic reactivity (e.g., asthma), and nasal polyps. Anaphylactoid reactions, like anaphylaxis, may have a fatal outcome.

Impaired Renal Function: Ketorolac tromethamine should be used with caution in patients with impaired renal function, or a history of kidney disease because it is a potent inhibitor of prostaglandin synthesis. Renal toxicity with ketorolac tromethamine has been seen in patients with conditions leading to a reduction in blood volume and/or renal blood flow where renal prostaglandins have a supportive role in the maintenance of renal perfusion. In these patients, administration of ketorolac tromethamine may cause a dose-dependent reduction in renal prostaglandin formation and may precipitate acute renal failure. Patients at greatest risk of this reaction are those with impaired renal function, dehydration, heart failure, liver dysfunction, those taking diuretics and the elderly. Discontinuation of ketorolac tromethamine therapy is usually followed by recovery to the pretreatment state.

Renal Effects: Ketorolac tromethamine and its metabolites are eliminated primarily by the kidneys, which, in patients with reduced creatinine clearance, will result in diminished clearance of the drug (see CLINICAL PHARMACOLOGY). Therefore, ketorolac tromethamine should be used with caution in patients with impaired renal function (see DOSAGE AND ADMINISTRATION) and such patients should be followed closely. With the use of ketorolac tromethamine, there have been reports of acute renal failure, interstitial nephritis, and nephrotic syndrome.

Because patients with underlying renal insufficiency are at increased risk of developing acute renal failure, the risks and benefits should be assessed prior to giving ketorolac tromethamine to these patients. Hence, in patients with moderately elevated serum creatinine, it is recommended that the daily dose of ketorolac tromethamine injection be reduced by half, not to exceed 60 mg/day. Ketorolac tromethamine is CONTRAINDICATED IN PATIENTS WITH SERUM CREATININE CONCENTRATIONS INDICATING ADVANCED RENAL IMPAIRMENT (see CONTRAINDICATIONS).

Hypovolemia should be corrected before treatment with ketorolac tromethamine is initiated.

Fluid Retention and Edema: Fluid retention, edema, retention of NaCl, oliguria, elevations of serum urea nitrogen and creatinine have been reported in clinical trials with ketorolac tromethamine. Therefore, ketorolac tromethamine should be used only very cautiously in patients with cardiac decompensation, hypertension, or similar conditions.

Pregnancy: In late pregnancy, as with other NSAIDs, ketorolac tromethamine should be avoided because it may cause premature closure of the ductus arteriosus.

PRECAUTIONS

GENERAL

Hepatic Effects: Ketorolac tromethamine should be used with caution in patients with impaired hepatic function, or a history of liver disease. Treatment with ketorolac tromethamine may cause elevations of liver enzymes, and in patients with pre-existing liver dysfunction it may lead to the development of a more severe hepatic reaction. The administration of ketorolac tromethamine should be discontinued in patients in whom an abnormal liver test has occurred as a result of ketorolac tromethamine therapy.

Hematologic Effects: Ketorolac tromethamine inhibits platelet aggregation and may prolong bleeding time; therefore, it is contraindicated as a pre-operative medication, and caution should be used when hemostasis is critical. Unlike aspirin, the inhibition of platelet function by ketorolac tromethamine disappears within 24 to 48 hours after the drug is discontinued. Ketorolac tromethamine does not appear to affect platelet count, prothrombin time (PT) or partial thromboplastin time (PTT). In controlled clinical studies, where ketorolac tromethamine was administered intramuscularly or intravenously postoperatively, the incidence of clinically significant postoperative bleeding was 0.4% for ketorolac tromethamine compared to 0.2% in the control groups receiving narcotic analgesics.

INFORMATION FOR PATIENTS

Ketorolac tromethamine is a potent NSAID and may cause serious side effects such as gastrointestinal bleeding or kidney failure, which may result in hospitalization and even fatal outcome.

Physicians, when prescribing ketorolac tromethamine, should inform their patients or their guardians of the potential risks of ketorolac tromethamine treatment (see Boxed WARNING, WARNINGS, PRECAUTIONS, and ADVERSE REACTIONS sections). Advise patients not to give ketorolac tromethamine tablets to other family members and to discard any unused drug.

Remember that the total duration of ketorolac tromethamine therapy is not to exceed 5 (five) days in adults or a single dose in pediatric patients ages 2 to 16 years.

DRUG INTERACTIONS

Ketorolac is highly bound to human plasma protein (mean 99.2%).

Warfarin, Digoxin, Salicylate and Heparin

The in vitro binding of warfarin to plasma proteins is only slightly reduced by ketorolac tromethamine (99.5% control vs 99.3%) when ketorolac plasma concentrations reach 5 to 10 mcg/mL. Ketorolac does not alter digoxin protein binding. In vitro studies indicate that, at therapeutic concentrations of salicylate (300 mcg/mL), the binding of ketorolac was reduced from approximately 99.2% to 97.5%, representing a potential two-fold increase in unbound ketorolac plasma levels. Therapeutic concentrations of digoxin, warfarin, ibuprofen, naproxen, piroxicam, acetaminophen, phenytoin, and tolbutamide did not alter ketorolac tromethamine protein binding.

In a study involving 12 volunteers, ketorolac tromethamine tablets were co-administered with a single dose of 25 mg warfarin, causing no significant changes in pharmacokinetics or pharmacodynamics of warfarin. In another study, ketorolac tromethamine injection was given with two doses of 5000 U of heparin to 11 healthy volunteers, resulting in a mean template bleeding time of 6.4 minutes (3.2 to 11.4 min) compared to a mean of 6.0 minutes (3.4 to 7.5 min) for heparin alone and 5.1 minutes (3.5 to 8.5 min) for placebo. Although these results do not indicate a significant interaction between ketorolac tromethamine and warfarin or heparin, the administration of ketorolac tromethamine to patients taking anticoagulants should be done extremely cautiously, and patients should be closely monitored (see WARNINGS and PRECAUTIONS).

Furosemide

Ketorolac tromethamine administered IV or IM reduced the diuretic response to furosemide in normovolemic healthy subjects by approximately 20% (mean sodium and urinary output decreased 17%).

Probenecid

Concomitant administration of ketorolac tromethamine tablets and probenecid resulted in decreased clearance of ketorolac and significant increases in ketorolac plasma levels (total AUC increased approximately 3-fold from 5.4 to 17.8 mcg/h/mL) and terminal half-life increased approximately 2-fold from 6.6 to 15.1 hours. Therefore, concomitant use of ketorolac tromethamine and probenecid is contraindicated.

Lithium

Inhibition of renal lithium clearance, leading to an increase in plasma lithium concentration, has been reported with some prostaglandin synthesis-inhibiting drugs. The effect of ketorolac tromethamine on plasma lithium has not been studied, but cases of increased lithium plasma levels during ketorolac tromethamine therapy have been reported.

Methotrexate

Concomitant administration of methotrexate and some NSAIDs has been reported to reduce the clearance of methotrexate, enhancing the toxicity of methotrexate. The effect of ketorolac tromethamine on methotrexate clearance has not been studied.

Nondepolarizing Muscle Relaxants

In postmarketing experience, there have been reports of a possible interaction between ketorolac tromethamine injection and nondepolarizing muscle relaxants that resulted in apnea. The concurrent use of ketorolac tromethamine with muscle relaxants has not been formally studied.

ACE Inhibitors

Concomitant use of ACE inhibitors may increase the risk of renal impairment, particularly in volume-depleted patients.

Antiepileptic Drugs

Sporadic cases of seizures have been reported during concomitant use of ketorolac tromethamine and antiepileptic drugs (phenytoin, carbamazepine).

Psychoactive Drugs

Hallucinations have been reported when ketorolac tromethamine was used in patients taking psychoactive drugs (fluoxetine, thiothixene, alprazolam).

Morphine

Ketorolac tromethamine injection has been administered concurrently with morphine in several clinical trials of postoperative pain without evidence of adverse interactions. Do not mix ketorolac tromethamine and morphine in the same syringe.

There is no evidence in animal or human studies that ketorolac tromethamine induces or inhibits hepatic enzymes capable of metabolizing itself or other drugs.

Carcinogenesis, Mutagenesis, and Impairment of Fertility

An 18-month study in mice with oral doses of ketorolac tromethamine at 2 mg/kg/day (0.9 times the human systemic exposure at the recommended IM or IV dose of 30 mg qid, based on area-under-the-plasma concentration curve [AUC]), and a 24-month study in rats at 5 mg/kg/day (0.5 times the human AUC), showed no evidence of tumorigenicity.

Ketorolac tromethamine was not mutagenic in the Ames test, unscheduled DNA synthesis and repair, and in forward mutation assays. Ketorolac tromethamine did not cause chromosome breakage in the in vivo mouse micronucleus assay. At 1590 mcg/mL and at higher concentrations, ketorolac tromethamine increased the incidence of chromosomal aberrations in Chinese hamster ovarian cells.

Impairment of fertility did not occur in male or female rats at oral doses of 9 mg/kg (0.9 times the human AUC) and 16 mg/kg (1.6 times the human AUC) of ketorolac tromethamine, respectively.

Pregnancy

Pregnancy Category C. Reproduction studies have been performed during organogenesis using daily oral doses of ketorolac tromethamine at 3.6 mg/kg (0.37 times the human AUC) in rabbits and at 10 mg/kg (1.0 times the human AUC) in rats. Results of these studies did not reveal evidence of teratogenicity to the fetus. Doses of ketorolac tromethamine tablets at 1.5 mg/kg (0.14 times the human AUC), administered after gestation day 17, caused dystocia and higher pup mortality in rats. There are no adequate and well-controlled studies of ketorolac tromethamine in pregnant women. Ketorolac tromethamine should be used during pregnancy only if the potential benefit justifies the potential risk to the fetus.

Labor and Delivery

The use of ketorolac tromethamine is contraindicatedin labor and delivery because, through its prostaglandin synthesis inhibitory effect, it may adversely affect fetal circulation and inhibit uterine contractions, thus increasing the risk of uterine hemorrhage (see CONTRAINDICATIONS).

Lactation and Nursing

After a single administration of a 10 mg ketorolac tromethamine tablet to humans, the maximum milk concentration observed was 7.3 ng/mL and the maximum milk-to-plasma ratio was 0.037. After one day of dosing (qid), the maximum milk concentration was 7.9 ng/mL and the maximum milk-to-plasma ratio was 0.025. Because of the possible adverse effects of prostaglandin-inhibiting drugs on neonates, use in nursing mothers is CONTRAINDICATED.

Pediatric Use

The safety and effectiveness of single doses of ketorolac tromethamine injection have been established in pediatric patients between the ages of 2 and 16 years. Ketorolac tromethamine injection has been shown to be effective in the management of moderately severe acute pain that requires analgesia at the opioid level, usually in a postoperative setting. Safety and efficacy in pediatric patients below the age of 2 have not been established. Therefore, ketorolac tromethamine injection is not recommended in pediatric patients below the age of 2. The risk of bleeding was greater in those patients administered ketorolac tromethamine injection following tonsillectomy. Physicians should consider the increased risk of bleeding before deciding to administer ketorolac tromethamine injection in patients following tonsillectomy (see WARNINGS: Hemorrhage and Pediatrics and Tonsillectomy).

The risks identified in the adult population with ketorolac tromethamine injection use also apply to pediatric patients. Therefore, consult the CONTRAINDICATIONS, WARNINGS, PRECAUTIONS, and ADVERSE REACTIONS sections when prescribing ketorolac tromethamine injection to pediatric patients.

Geriatric Use (≥65 Years of Age)

Because ketorolac tromethamine may be cleared more slowly by the elderly (see CLINICAL PHARMACOLOGY) who are also more sensitive to the adverse effects of NSAIDs (see WARNINGS − Renal Effects), extra caution and reduced dosages (see DOSAGE AND ADMINISTRATION) must be used when treating the elderly with ketorolac tromethamine injection. The lower end of the ketorolac tromethamine injection dosage range is recommended for patients over 65 years of age and total daily dose is not to exceed 60 mg. The incidence and severity of gastrointestinal complications increases with increasing dose of, and duration of treatment with, ketorolac tromethamine.

ADVERSE REACTIONS

Adverse reaction rates increase with higher doses of ketorolac tromethamine. Practitioners should be alert for the severe complications of treatment with ketorolac tromethamine, such as G.I. ulceration, bleeding and perforation, postoperative bleeding, acute renal failure, anaphylactic and anaphylactoid reactions, and liver failure (see Boxed WARNING, WARNINGS, PRECAUTIONS, and DOSAGE AND ADMINISTRATION). These NSAID-related complications can be serious in certain patients for whom ketorolac tromethamine is indicated, especially when the drug is used inappropriately.

The Adverse Reactions Listed Below Were Reported In Clinical Trials As Probably Related To KETOROLAC TROMETHAMINE.

Incidence Greater Than 1%

(Percentage of incidence in parentheses for those events reported in 3% or more patients)

Body as a Whole: edema (4%).

Cardiovascular: hypertension.

Dermatologic: pruritus, rash.

Gastrointestinal: nausea (12%), dyspepsia (12%), gastrointestinal pain (13%), diarrhea (7%), constipation, flatulence, gastrointestinal fullness, vomiting, stomatitis.

Hemic and Lymphatic: purpura.

Nervous System: headache (17%), drowsiness (6%), dizziness (7%), sweating.

Injection-site pain was reported by 2% of patients in multi-dose studies.

Incidence 1% or Less

Body as a Whole: weight gain, fever, infections, asthenia.

Cardiovascular: palpitation, pallor, syncope.

Dermatologic: urticaria.

Gastrointestinal: gastritis, rectal bleeding, eructation, anorexia, increased appetite.

Hemic and Lymphatic: epistaxis, anemia, eosinophilia.

Nervous System: tremors, abnormal dreams, hallucinations, euphoria, extrapyramidal symptoms, vertigo, paresthesia, depression, insomnia, nervousness, excessive thirst, dry mouth, abnormal thinking, inability to concentrate, hyperkinesis, stupor.

Respiratory: dyspnea, pulmonary edema, rhinitis, cough.

Special Senses: abnormal taste, abnormal vision, blurred vision, tinnitus, hearing loss.

Urogenital: hematuria, proteinuria, oliguria, urinary retention, polyuria, increased urinary frequency.

The Following Adverse Events Were Reported From Postmarketing Experience.

Body as a Whole: hypersensitivity reactions such as anaphylaxis, anaphylactoid reaction, laryngeal edema, tongue edema (see Boxed WARNING, WARNINGS), angioedema, myalgia.

Cardiovascular: hypotension and flushing.

Dermatologic: Lyell’s syndrome, Stevens-Johnson syndrome, exfoliative dermatitis, maculo-papular rash, urticaria.

Gastrointestinal: peptic ulceration, G.I. hemorrhage, G.I. perforation (see Boxed WARNING, WARNINGS), melena, acute pancreatitis, hematemesis, esophagitis.

Hemic and Lymphatic: postoperative wound hemorrhage rarely requiring blood transfusion (see Boxed WARNING, WARNINGS and PRECAUTIONS), thrombocytopenia, leukopenia.

Hepatic: hepatitis, liver failure, cholestatic jaundice.

Nervous System: convulsions, psychosis, aseptic meningitis.

Respiratory: asthma, bronchospasm.

Urogenital: acute renal failure (see Boxed WARNING, WARNINGS), flank pain with or without hematuria and/or azotemia, nephritis, hyponatremia, hyperkalemia, hemolytic uremic syndrome.

OVERDOSAGE

Symptoms following acute NSAIDs overdoses are usually limited to lethargy, drowsiness, nausea, vomiting, and epigastric pain, which are generally reversible with supportive care. Gastrointestinal bleeding can occur. Hypertension, acute renal failure, respiratory depression and coma may occur, but are rare. Anaphylactoid reactions have been reported with therapeutic ingestion of NSAIDs, and may occur following an overdose.

Patients should be managed by symptomatic and supportive care following a NSAIDs overdose. There are no specific antidotes. Emesis and/or activated charcoal (60 g to 100 g in adults, 1 g/kg to 2 g/kg in children) and/or osmotic cathartic may be indicated in patients seen within 4 hours of ingestion with symptoms or following a large oral overdose (5 to 10 times the usual dose).

In controlled overdosage, daily doses of 360 mg of ketorolac tromethamine injection given for 5 days (three times the highest recommended dose), caused abdominal pain and peptic ulcers which healed after discontinuation of dosing. Metabolic acidosis has been reported following intentional overdosage.

Single overdoses of ketorolac tromethamine have been variously associated with abdominal pain, nausea, vomiting, hyperventilation, peptic ulcers and/or erosive gastritis and renal dysfunction which have resolved after discontinuation of dosing. Dialysis does not significantly clear ketorolac tromethamine from the blood stream.

DOSAGE AND ADMINISTRATION

IN ADULTS, THE COMBINED DURATION OF USE OF KETOROLAC TROMETHAMINE INJECTION AND KETOROLAC TROMETHAMINE TABLET IS NOT TO EXCEED 5 DAYS. IN ADULTS, THE USE OF KETOROLAC TROMETHAMINE TABLETS IS ONLY INDICATED AS CONTINUATION THERAPY TO KETOROLAC TROMETHAMINE INJECTION.

KETOROLAC TROMETHAMINE INJECTION

Adult Patients: Ketorolac tromethamine injection may be used as a single or multiple dose, on a regular or prn schedule for the management of moderately severe, acute pain that requires analgesia at the opioid level, usually in a postoperative setting. Hypovolemia should be corrected prior to the administration of ketorolac tromethamine (see WARNINGS − Renal Effects). Patients should be switched to alternative analgesics as soon as possible, but ketorolac tromethamine therapy is not to exceed 5 days.

When administering ketorolac tromethamine, the IV bolus must be given over no less than 15 seconds. The IM administration should be given slowly and deeply into the muscle. The analgesic effect begins in ~30 minutes with maximum effect in 1 to 2 hours after dosing IV or IM. Duration of analgesic effect is usually 4 to 6 hours.

Single-Dose Treatment: The following regimen should be limited to single administration use only.

Adult Patients:

IM Dosing:

Patients <65 years of age: One dose of 60 mg.
Patients ≥65 years of age, renally impaired and/or less than 50 kg (110 lbs) of body weight: One dose of 30 mg.

IV Dosing:

Patients <65 years of age: One dose of 30 mg.
Patients ≥65 years of age, renally impaired and/or less than 50 kg (110 lbs) of body weight: One dose of 15 mg.

Pediatric Patients (2 to 16 years of age): The pediatric population should receive only a single dose of ketorolac tromethamine injection as follows:

IM Dosing:

One dose of 1 mg/kg up to a maximum of 30 mg.

IV Dosing:

One dose of 0.5 mg/kg up to a maximum of 15 mg.

Multiple-Dose Treatment (IV or IM):

Patients <65 years of age: The recommended dose is 30 mg ketorolac tromethamine injection every 6 hours. The maximum daily dose should not exceed 120 mg.

For patients ≥65 years of age, renally impaired patients (see WARNINGS), and patients less than 50 kg (110 lbs): The recommended dose is 15 mg ketorolac tromethamine injection every 6 hours. The maximum daily dose for these populations should not exceed 60 mg.

For breakthrough pain, do not increase the dose or the frequency of ketorolac tromethamine. Consideration should be given to supplementing these regimens with low doses of opioids “prn” unless otherwise contraindicated.

Pharmaceutical Information for Ketorolac Tromethamine Injection:

Ketorolac tromethamine should not be mixed in a small volume (e.g., in a syringe) with morphine sulfate, meperidine hydrochloride, promethazine hydrochloride or hydroxyzine hydrochloride; this will result in precipitation of ketorolac from solution.

Parenteral drug products should be inspected visually for particulate matter and discoloration prior to administration, whenever solution and container permit.

HOW SUPPLIED

Ketorolac Tromethamine Injection, USP for intramuscular and intravenous use is available in an iSecureTM sterile cartridge unit:

30 mg: 30 mg/mL, 1 mL iSecure sterile cartridge unit (with Luer Lock) boxes of:

10 NDC 21695-588-10

25 NDC 21695-588-10

Store at 20 to 25°C (68 to 77°F). [See USP Controlled Room Temperature.] Retain in carton until time of use.

PROTECT FROM LIGHT.

Revised: March, 2007

Directions for iSecure Syringe

1. To release plunger rod, grasp syringe and depress rod until it releases from the syringe.

2. Attach plunger rod to the syringe barrel by inserting rod into the plunger end and turning clockwise.

3. Remove luer tip cover. Attach needle or blunt cannula if applicable.

4. Expel air by pushing on the plunger rod. Do not touch the syringe tip. Administer Drug.

Note: To prevent needlestick injuries, needles and blunt cannulas should not be recapped, purposely bent, or broken by hand.

Printed in USA

EN-1465

Hospira, Inc., Lake Forest, IL 60045 USA

Packaged by:

Rebel Distributors Corp

Thousand Oaks, CA 91320